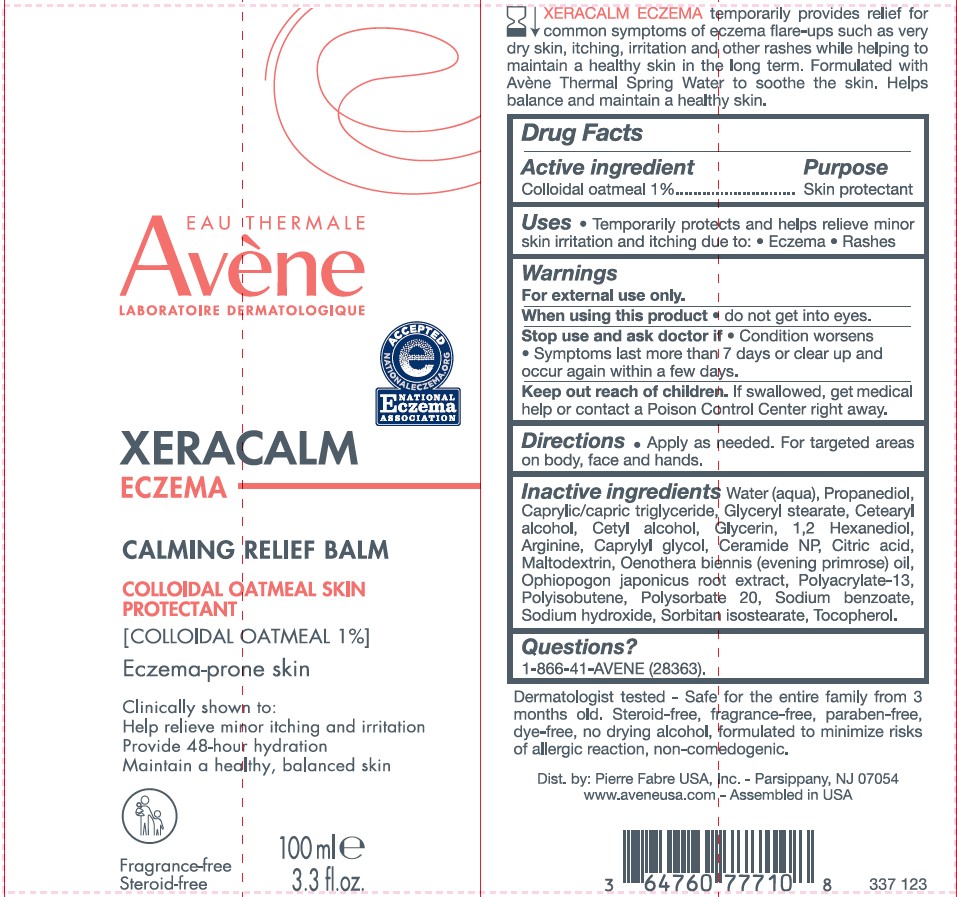 DRUG LABEL: Avene XERACALM Eczema Calming Relief Balm
NDC: 64760-777 | Form: CREAM
Manufacturer: Pierre Fabre USA Inc.
Category: otc | Type: HUMAN OTC DRUG LABEL
Date: 20241106

ACTIVE INGREDIENTS: OATMEAL 1 g/100 g
INACTIVE INGREDIENTS: POLYSORBATE 20; SORBITAN ISOSTEARATE; SODIUM BENZOATE; 1,2-HEXANEDIOL; WATER; CETOSTEARYL ALCOHOL; ARGININE; CAPRYLYL GLYCOL; PROPANEDIOL; GLYCERYL MONOSTEARATE; CETYL ALCOHOL; GLYCERIN; ACONITIC ACID; MALTODEXTRIN; EVENING PRIMROSE OIL; POLYACRYLATE-13; POLYISOBUTYLENE (1000 MW); OPHIOPOGON JAPONICUS ROOT; TOCOPHEROL; CERAMIDE NP; SODIUM HYDROXIDE; MEDIUM-CHAIN TRIGLYCERIDES

Avene XERACALM Eczema Calming Relief Balm

Active ingredient

Colloidal oatmeal 1%

Purpose

Skin protectant

Uses

Temporarily protects and helps relieve minor skin irritation and itching due to:

- Eczema
- Rashes

Warnings

For external use only.

When using this product - do not get into eyes

Stop use and ask a doctor if

- Condition worsens
- Symptoms last more than 7 days or clear up and occur again within a few days

Keep out of reach of children. If swallowed, get medical help or contact a Poison Control Center right away.

Directions

- Apply as needed. For targeted areas on body, face and hands.

Inactive ingredients

Water (aqua), Propanediol, Caprylic/capric triglyceride, Glyceryl stearate, Cetearyl alcohol, Cetyl alcohol, Glycerin, 1,2 Hexanediol, Arginine, Caprylyl glycol, Ceramide NP, Citric acid, Maltodextrin, Oenothera biennis (evening primrose) oil, Ophiopogon japonicus root extract, Polyacrylate-13, Polyisobutene, Polysorbate 20, Sodium benzoate, Sodium hydroxide, Sorbitan isostearate, Tocopherol.

Questions?

1-866-41-AVENE (28363).